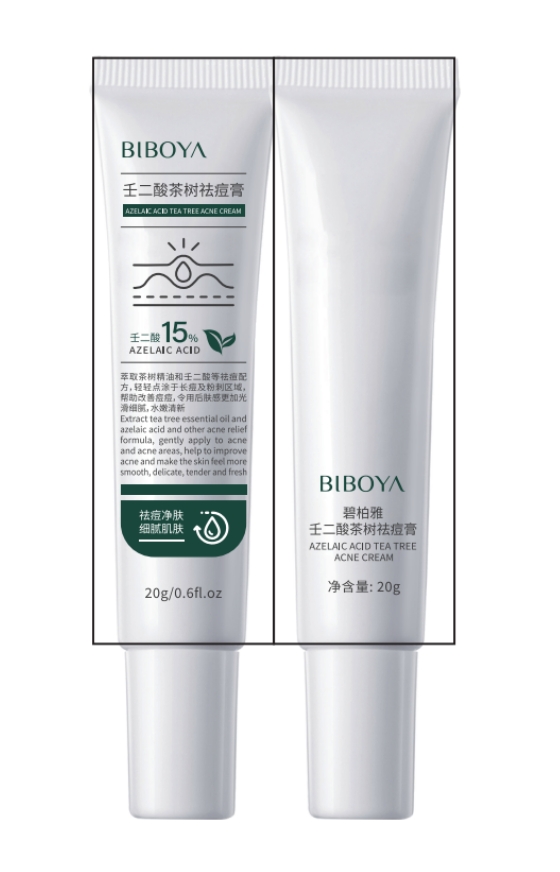 DRUG LABEL: BIBOYA Azelaic Acid Tea Tree Acne Cream
NDC: 84507-005 | Form: CREAM
Manufacturer: Guangdong Miaolian Cosmetics Co., Ltd.
Category: otc | Type: HUMAN OTC DRUG LABEL
Date: 20240815

ACTIVE INGREDIENTS: ALLANTOIN 0.197 mg/100 g; SALICYLIC ACID 0.28 mg/100 g; GLYCERIN 3 mg/100 g; AZELAIC ACID 0.2 mg/100 g
INACTIVE INGREDIENTS: AMINO ACIDS; BIFIDOBACTERIUM BIFIDUM; PENTYLENE GLYCOL; YEAST; WATER; TRIETHYLSILANE; ETHYLHEXYLGLYCERIN; EDETATE DISODIUM; PANTHENOL; XANTHAN GUM; PROPANEDIOL; UREA; FOLIC ACID; ACRYLATES/C10-30 ALKYL ACRYLATE CROSSPOLYMER (60000 MPA.S); BACILLUS AMYLOLIQUEFACIENS; C13-14 ISOPARAFFIN; HEXYLENE GLYCOL; LAURETH-7; DEXTRIN, CORN; .ALPHA.-TOCOPHEROL ACETATE

DOSAGE AND ADMINISTRATION

1.Cleanse the skin thoroughly before applying the product
2.Apply to affected areas with a thin layer, one to three timesdaily or as directed by a doctor

WARNINGS

For external use only

INACTIVE INGREDIENT

Water,1,3-propanediol, dextrin, triethyl, acrylates /C10-30 alkyl acrylate crosslinked polymer, panthenol, tocopherol acetate, urea, C13-14 iso-alkanes,ethyl hexyl glycerol, lauryl ether 7, EDTA Disodium,Sesame amino acids, Xanthan gum, bifida yeast fermentation product filtrate, 1,2-pentanediol, 1,2-hexanediol, Bacillus clostridium/Soybean fermentation product extract, folic acid, yeast fermentation product extract

INDICATIONS AND USAGE

Acne Treatment

1,Treats and controls symptoms of Acne
2,Reduces redness and inflammation associated with Acne
3,Promotes even skin tone
4,Minimizes the appearance of blood vessels

KEEP OUT OF REACH OF CHILDREN

lf swallowed, get medical help orcontact Poison Control Center right away.

WHEN USING

Avoid contact with eyes, If contact occurs,rinse eyes thoroughly with water

PURPOSE

Acne Treatment